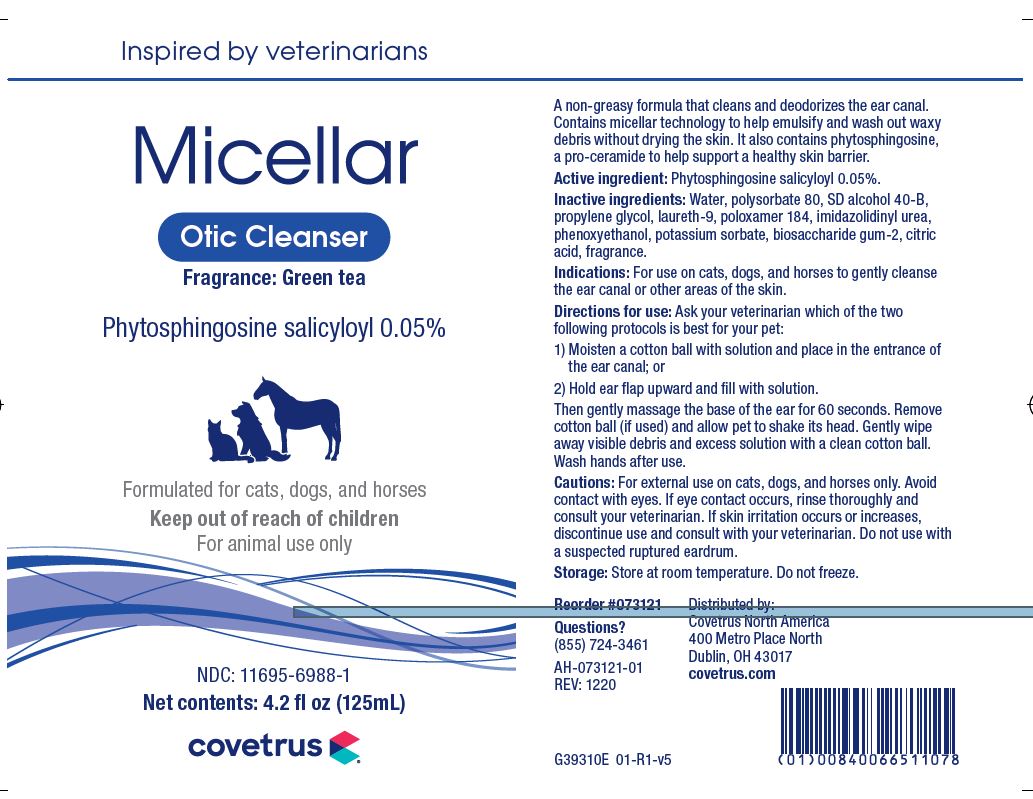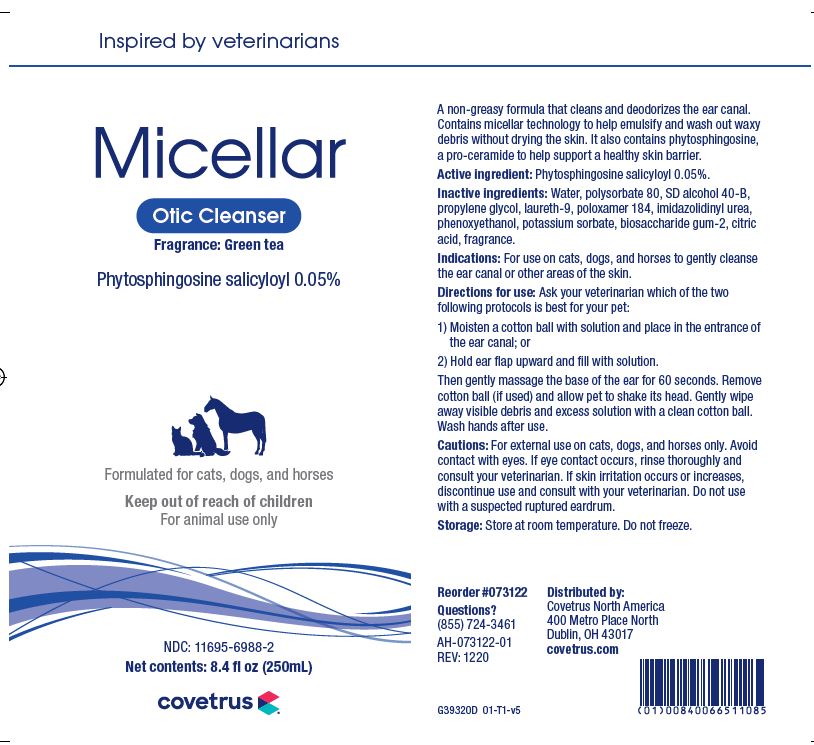 DRUG LABEL: MICELLAR
NDC: 11695-6988 | Form: SOLUTION
Manufacturer: Butler Animal Health Supply, LLC dba Covetrus North America
Category: animal | Type: OTC ANIMAL DRUG LABEL
Date: 20220523

ACTIVE INGREDIENTS: SALICYLOYL PHYTOSPHINGOSINE .5 mg/1 mL
INACTIVE INGREDIENTS: WATER; ALCOHOL; POLYSORBATE 80; PROPYLENE GLYCOL; LAURETH-9 PHOSPHATE; POLOXAMER 184; BIOSACCHARIDE GUM-2; IMIDUREA; PHENOXYETHANOL; POTASSIUM SORBATE; CITRIC ACID MONOHYDRATE

MICELLAR OTIC CLEANSER

DESCRIPTION

Micellar Otic Cleanser

Phytosphingosine Salicyloyl 0.05%

A non-greasy formula that cleans and deodorizes the ear canal. Contains micellar technology to help emulsify and wash out waxy debris without drying the skin. It also contains phytosphingosine, a pro-ceramide to help support a healthy skin barrier.

Active Ingredient: Phytosphingosine Salicyloyl 0.05%

Inactive Ingredients: Water, polysorbate 80, SD alcohol 40-B, propylene glycol, laureth-9, poloxamer 184, imidazolidinyl urea, phenoxyethanol, potassium sorbate, biosaccharide gum-2, citric acid, fragrance.

INDICATIONS AND USAGE

Indications: For use in cats, dogs, and horses to gently cleanse the ear canal or other areas of the skin.

Directions for use: Ask your veterinarian which of the two following protocols is best for your pet:

1) Moisten a cotton ball with solution and place in the entrance of the ear canal; OR

2) Hold the ear flap upward and fill with solution.

Then gently massage the base of the ear for 60 seconds. Remove cotton ball (if used) and allow pet to shake its head. Gently wipe away visible debris and excess solution with a clean cotton ball. Wash hands after use.

WARNINGS AND PRECAUTIONS

Cautions: For external use on cats, dogs, and horses only. Avoid contact with eyes. If eye contact occurs, rinse thoroughly and consult with your veterinarian. If skin irritation occurs or increases, discontinue use and consult with your veterinarian. Do not use with a suspected ruptured eardrum.

Storage: Store at room temperature. Do not freeze.

Reorder #073122

Questions? (855) 724-3461

Distributed by:

Covetrus North America

400 Metro Place North

Dublin, OH 43017

covetrus.com

PRINCIPAL DISPLAY PANEL - 125 mL BOTTLE

Micellar

Otic Cleanser

Fragrance: Green tea

Phytosphingosine salicyloyl 0.05%

Formulated for cats, dogs, and horses

Keep out of reach of children

For animal use only

NDC: 11695-6988-1

Net contents: 4.2 fl oz (125mL)

covetrus

PRINCIPAL DISPLAY PANEL - 250 mL BOTTLE

Micellar

Otic Cleanser

Fragrance: Green tea

Phytosphingosine salicyloyl 0.05%

Formulated for cats, dogs, and horses

Keep out of reach of children

For animal use only

NDC: 11695-6988-2

Net contents: 8.4 fl oz (250mL)

covetrus